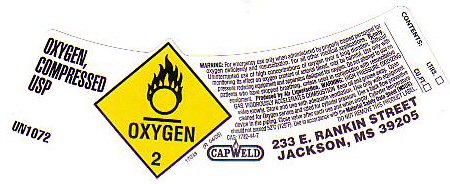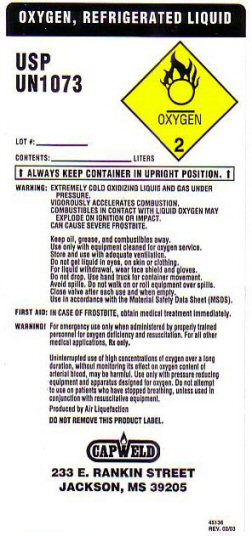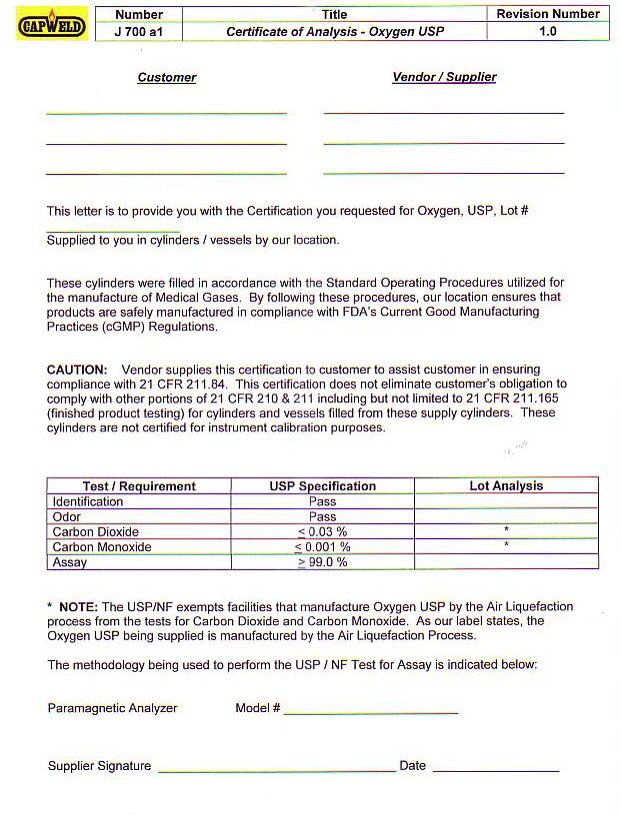 DRUG LABEL: OXYGEN
NDC: 52849-100 | Form: GAS
Manufacturer: Capweld Inc
Category: prescription | Type: HUMAN PRESCRIPTION DRUG LABEL
Date: 20100101

ACTIVE INGREDIENTS: Oxygen 99 L/100 L

OXYGEN COMPRESSED LABEL

OXYGEN COMPRESSED USP UN 1072

PRODUCED BY AIR LIQUEFACTION

WARNING: HIGH PRESSURE OXIDIZING GAS VIGOROUSLY ACCELERATES COMBUSTION. KEEP OIL AND GREASE AWAY. OPEN VALVE SLOWLY. STORE AND USE WITH ADEQUATE VENTILATION. USE ONLY WITH EQUIPMENT CLEANED FOR OXYGEN SERVICE AND RATED FOR CYLINDER PRESSURE. USE ONLY WITH PRESSURE REDUCING EQUIPMENT AND APPARATUS DESIGNED FOR OXYGEN SERVICE. USE A BACK FLOW PREVENTATIVE IN THE PIPING. CLOSE VALVE AFTER EACH USE AND WHEN EMPTY. CYLINDER TEMPERATURES SHOULD NOT EXCEED 52 C (125 F) USE IN ACCORDANCE WITH MATERIAL SAFETY DATA SHEET (MSDS)

.

GENERAL WARNINGS AND PRECAUTIONS

Warning: for emergency use only when administered by properly trained personnel for oxygen deficiency and resuscitation. For all other medical applications Rx Only. Uninterrupted use of high concentrations of oxygen over a long duration without monitoring oxygen content of arterial blood may be harmful. Uninterrupted use of high concentrations of oxygen for more than 5 hours may be harmful. Do not attempt to use on patients who have stopped breathing, unless used in conjunction with resuscitative equipment.

DO NOT REMOVE THIS PRODUCT LABEL

OXYGEN REFRIGERATED LIQUID LABEL

OXYGEN REFRIGERATED LIQUID U.S.P. UN 1073
ALWAYS KEEP CONTAINER IN UPRIGHT POSITION
WARNING: EXTREMELY COLD OXIDIZING LIQUID AND GAS UNDER PRESSURE. VIGOROUSLY ACCELERATES COMBUSTION. COMBUSTIBLES IN CONTACT WITH LIQUID OXYGEN MAY EXPLODE ON IGNITION OR IMPACT. CAN CAUSE SEVERE FROSTBITE. STORE AND USE WITH ADEQUATE VENTILATION. KEEP OIL, GREASE, AND COMBUSTIBLES AWAY. NO SMOKING IN CONTAINER AREA. DO NOT USE OR STORE NEAR HEAT OR OPEN FLAME. USE ONLY WITH EQUIPMENT CLEANED FOR OXYGEN SERVICE. DO NOT GET LIQUID IN EYES ON SKIN OR CLOTHING. FOR LIQUID WITHDRAWAL, WEAR FACE SHIELD AND GLOVES. DO NOT DROP USE HAND TRUCK FOR CONTAINER MOVEMENT. AVOID SPILLS. DO NOT WALK ON OR ROLL EQUIPMENT OVER SPILLS. CLOSE VALVE AFTER EACH USE AND WHEN EMPTY. USE IN ACCORDANCE WITH MATERIAL SAFETY DATA SHEET (MSDS).
FIRST AID: IN CASE OF FROSTBITE OBTAIN MEDICAL TREATMENT IMMEDIATELY.

OXYGEN CERTIFICATE OF ANALYSIS

CUSTOMER ___________________ VENDOR / SUPPLIER ________________________ THIS LETTER IS TO PROVIDE YOU WITH THE
CERTIFICATION YOU REQUESTED FOR OXYGEN USP LOT NUMBER _______________________ SUPPLIED TO YOU IN
CYLINDERS / VESSELS BY OUR LOCATION
These cylinders were filled in accordance with the Standard Operating
Procedures utilized for the manufacture of Medical Gases. By
following these procedures, our location ensures that products are
safely manufactured in compliance with FDA’s Current Good Manufacturing
Practices
(cGMP) Regulations.
CAUTION: VENDOR SUPPLIES THIS CERTIFICATION TO CUSTOMER TO ASSIST
CUSTOMER IN ENSURING COMPLIANCE WITH 21 CFR 211.84. THIS
CERTIFICATION DOES NOT ELIMINATE CUSTOMERS OBLIGATION TO COMPLY WITH
OTHER PORTIONS OF 21 CFR 210 AND 211, INCLUDING BUT NOT
LIMITED TO 21 CFR 211.165 (FINISHED PRODUCT TESTING) FOR CYLINDERS AND
VESSELS FILLED FROM THESE SUPPLY CYLINDERS. THESE CYLINDERS ARE
NOT CERTIFIED FOR INSTRUMENT CALIBRATION.
TEST REQUIREMENT USP SPECIFICATION LOT ANALYSIS
IDENTIFICATION PASS
ODOR PASS
CARBON DIOXIDE LESS THAT 0.03%
CARBON MONOXIDE LESS THAT 0.001%
ASSAY GREATER THAN 99.0%
*
NOTE: The USP/NF exempts facilities that manufacture Oxygen USP by the
Air Liquefaction process from the tests for Carbon Dioxide and Carbon
Monoxide.
As our label states, the Oxygen USP being supplied is manufactured by the Air Liquefaction Process.
The methodology being used to perform the USP / NF Test for
Assay is indicated below: Paramagnetic Analyzer Model # _________________________
J 700 a1
REVISION 1.0
CERTIFICATE OF ANALYSIS - OXYGEN USP